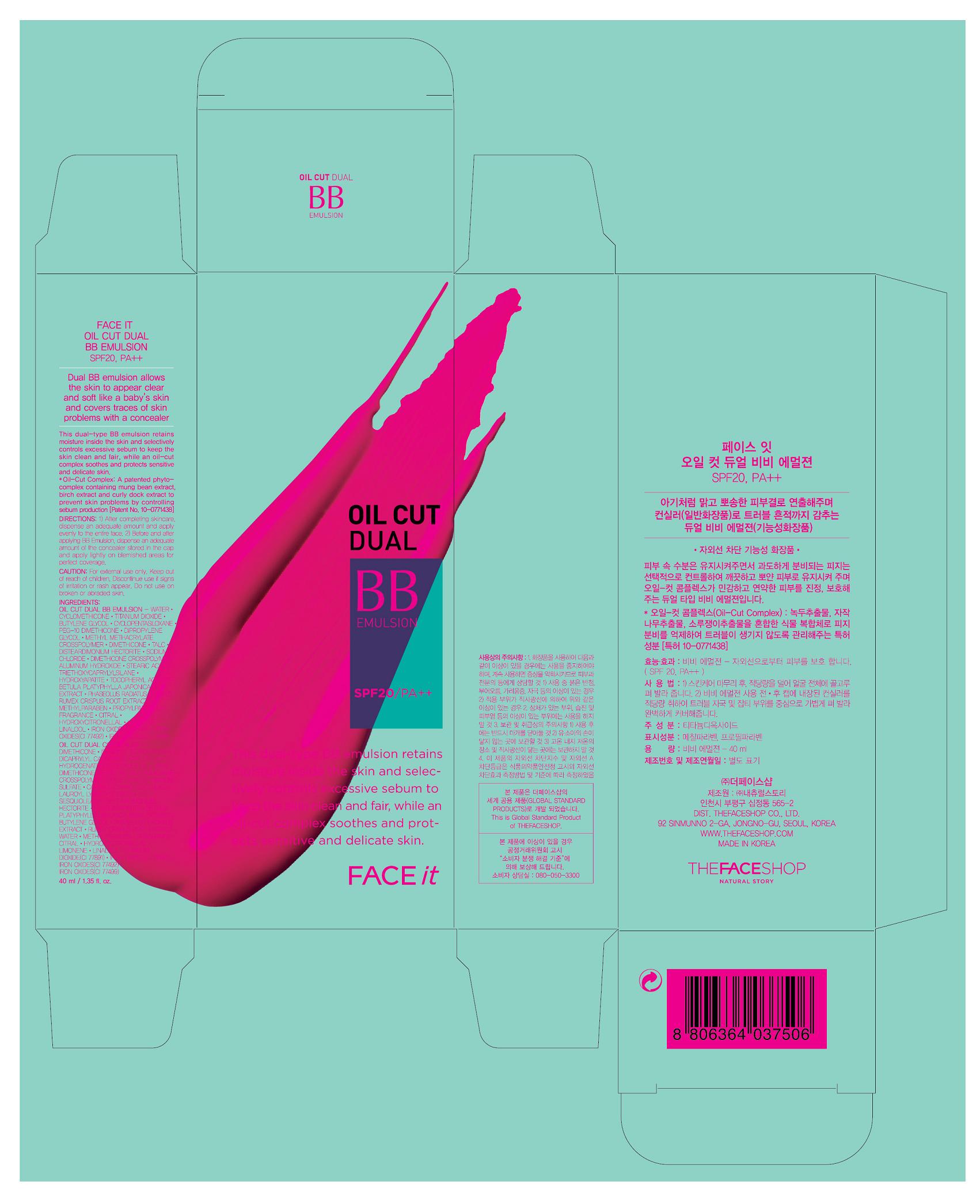 DRUG LABEL: FACE IT OIL CUT DUAL BB EMULSION SPF20
NDC: 51523-111 | Form: CREAM
Manufacturer: THEFACESHOP CO., LTD
Category: otc | Type: HUMAN OTC DRUG LABEL
Date: 20110901

ACTIVE INGREDIENTS: TITANIUM DIOXIDE 10 mL/100 mL
INACTIVE INGREDIENTS: WATER; TRIETHOXYCAPRYLYLSILANE; CYCLOMETHICONE; BUTYLENE GLYCOL; CYCLOMETHICONE 5; ALUMINUM HYDROXIDE; STEARIC ACID; DIPROPYLENE GLYCOL; DIMETHICONE; TALC; SODIUM CHLORIDE; METHYLPARABEN; PROPYLPARABEN; FERRIC OXIDE RED; FERRIC OXIDE YELLOW; FERROSOFERRIC OXIDE; TRIBASIC CALCIUM PHOSPHATE; BETULA PLATYPHYLLA VAR. JAPONICA BARK; RUMEX CRISPUS ROOT; CITRAL; HYDROXYCITRONELLAL; LINALOOL, (+/-)-; MUNG BEAN

Drug Facts

ACTIVE INGREDIENT

TITANIUM DIOXIDE (10%)

INACTIVE INGREDIENT

WATER
TRIETHOXYCAPRYLYLSILANE
CYCLOMETHICONE
BUTYLENE GLYCOL
CYCLOMETHICONE 5
ALUMINUM HYDROXIDE
STEARIC ACID
DIPROPYLENE GLYCOL
DIMETHICONE
TALC
SODIUM CHLORIDE
METHYLPARABEN
PROPYLPARABEN
FERRIC OXIDE RED
FERRIC OXIDE YELLOW
FERROSOFERRIC OXIDE
TRIBASIC CALCIUM PHOSPHATE
BETULA PLATYPHYLLA VAR. JAPONICA BARK
RUMEX CRISPUS ROOT
CITRAL
HYDROXYCITRONELLAL
LINALOOL, (+/-)-
MUNG BEAN

PURPOSE

Provides high protection against sunburn and tanning.

WHEN USING

Avoid contact with eyes.

STOP USE

Discontinue use if sign of irritation or rash appear.

DOSAGE AND ADMINISTRATION

Dispense an adequate amount and apply evenly. (At the final stage of basic skincare, dispense an adequate amount and apply evenly to desired parts)

PACKAGE LABEL

FACE IT OIL CUT DUAL BB EMULSION SPF20, PA++